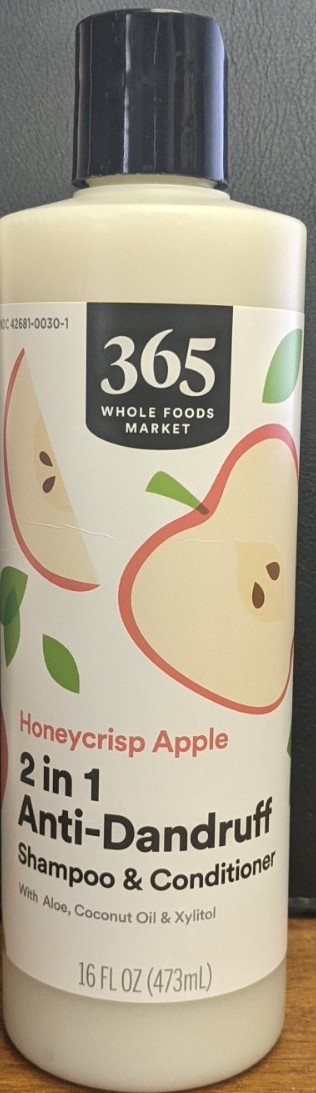 DRUG LABEL: AntiDandruffShampooConditioner
NDC: 42681-0030 | Form: SHAMPOO
Manufacturer: Whole Foods Market, Inc.
Category: otc | Type: HUMAN OTC DRUG LABEL
Date: 20250429

ACTIVE INGREDIENTS: SALICYLIC ACID 3 mg/100 mL
INACTIVE INGREDIENTS: WATER 73.32 mL/100 mL

365 Anti-Dandruff Shampoo & Conditioner 2 in 1

Active Ingredients

Active Ingredients Purpose

Salicylic Acid 3% Anti-Dandruff

Use

Helps prevent recurrence of flaking and itching associated with dandruff.

Warning

Avoid contact with eyes.

If contact occurs, rinse eyes thoroughly with water.

Stop use and ask a doctor If the condition worsens or does not improve after regular use of this product as directed.

For external use only.

Keep out of the reach of children. If swallowed, get medical help or contact Poison Control Center right away

Directions

For best results use at least twice a week or as directed by a doctor.

For maximum dandruff control, use every time you wash your hair.

Shake before use. Wet hair, massage into scalp and rinse. Repeat if desired.

Other Information

Store in a cool, dry place.

Inactive Ingredients

WATER, COCAMIDOPROPYL BETAINE, SODIUM COCO-SULFATE, AMMONIUM LAURYL SULFATE, GLYCERIN, GLYCOL STEARATE, ALOE BARBADENSIS LEAF JUICE, COCO-BETAINE, GLUCONOLACTONE, FRAGRANCE, BENZYL ALCOHOL, POLYQUATERNIUM-7, SODIUM BENZOATE, POTASSIUM SORBATE, COCOS NUCIFERA (COCONUT) OIL, CITRIC ACID, XYLITOL, TRIETHYL CITRATE, COCONUT ALKANES, COCO-CAPRYLATE/CAPRATE, GUAR HYDROXYPROPYLTRIMONIUM CHLORIDE, DECYL GLUCOSIDE, HYDROLYZED QUINOA, PRUNUS AMYGDALUS DULCIS (SWEET ALMOND) OIL, SIMMONDSIA CHINENSIS (JOJOBA) SEED OIL

Questions, Comments?

1-844-WFM-TALK (1-844-936-8255)

Purpose

Anti-Dandruff

Keep out of reach of children. If swallowed, get medical help or contact Poison Control Center right away.

Use

For best results use at least twice a week or as directed by a doctor.

For maximum dandruff control, use every time you wash your hair.

Shake before use. Wet hair, massage into scalp and rinse. Repeat if desired.

DOSAGE AND ADMINISTRATION

Use every time you wash your hair.